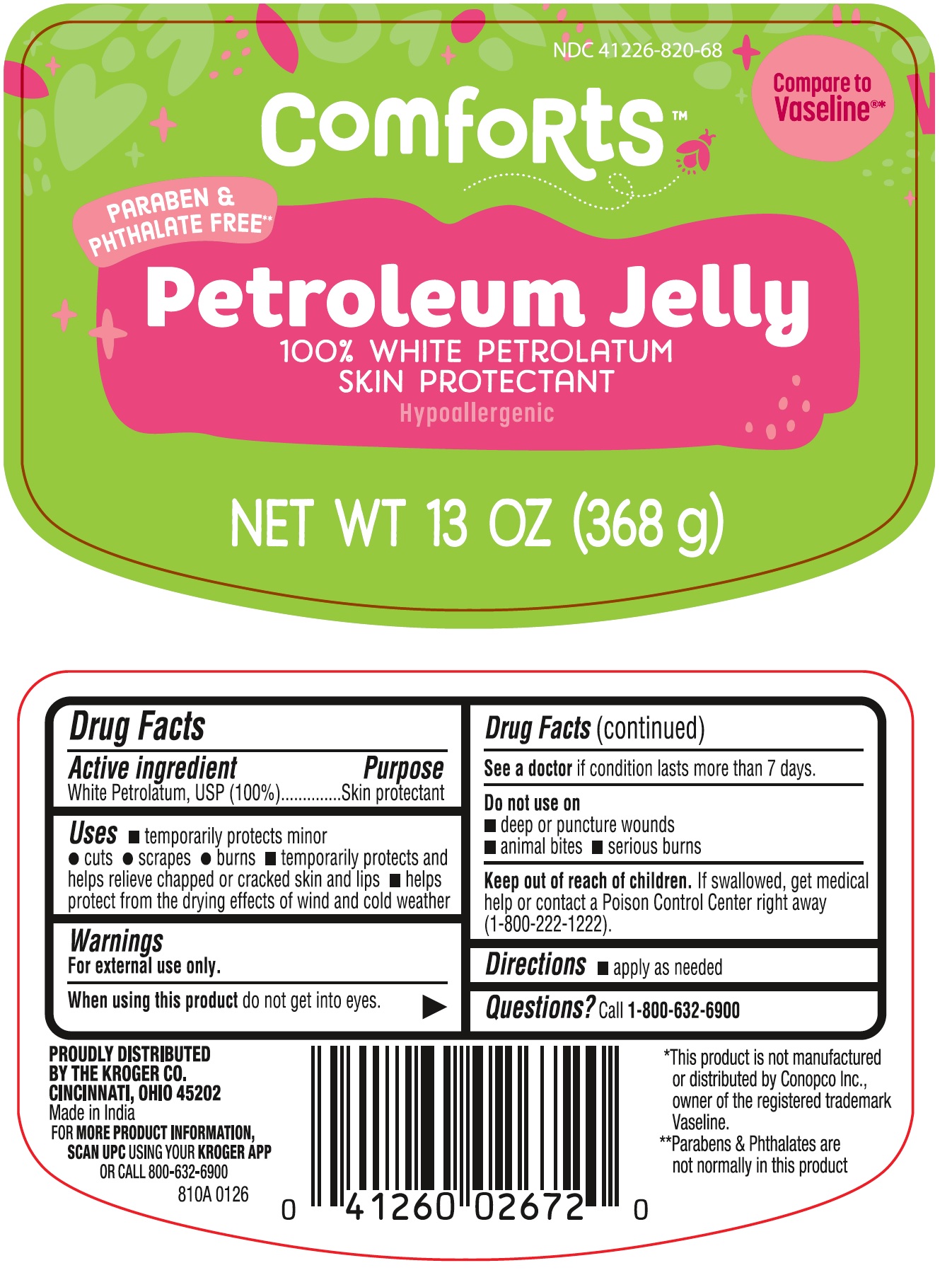 DRUG LABEL: Comforts Petroleum Jelly
NDC: 41226-820 | Form: JELLY
Manufacturer: KROGER
Category: otc | Type: HUMAN OTC DRUG LABEL
Date: 20260203

ACTIVE INGREDIENTS: PETROLATUM 1 g/1 g

Kroger Comforts Petroleum Jelly

Drug Facts

-

Active ingredient

White Petrolatum, USP (100%)

Purpose

Skin protectant

Uses

- temporarily protects minor

-cuts
-scrapes
-burns

- temporarily protects and helps relieve chapped or cracked skin and lips
- helps protect from the drying effects of wind and cold weather

Warnings

For external use only.

When using this product do not get into eyes.

See a doctor if condition lasts more than 7 days.

Do not use on

- deep or puncture wounds
- animal bites
- serious burns

Keep out of reach of children.

If swallowed, get medical help or contact a Poison Control Center right away (1-800-222-1222).

Directions

- apply as needed

INACTIVE INGREDIENT

-

Questions?

Call 1-800-632-6900